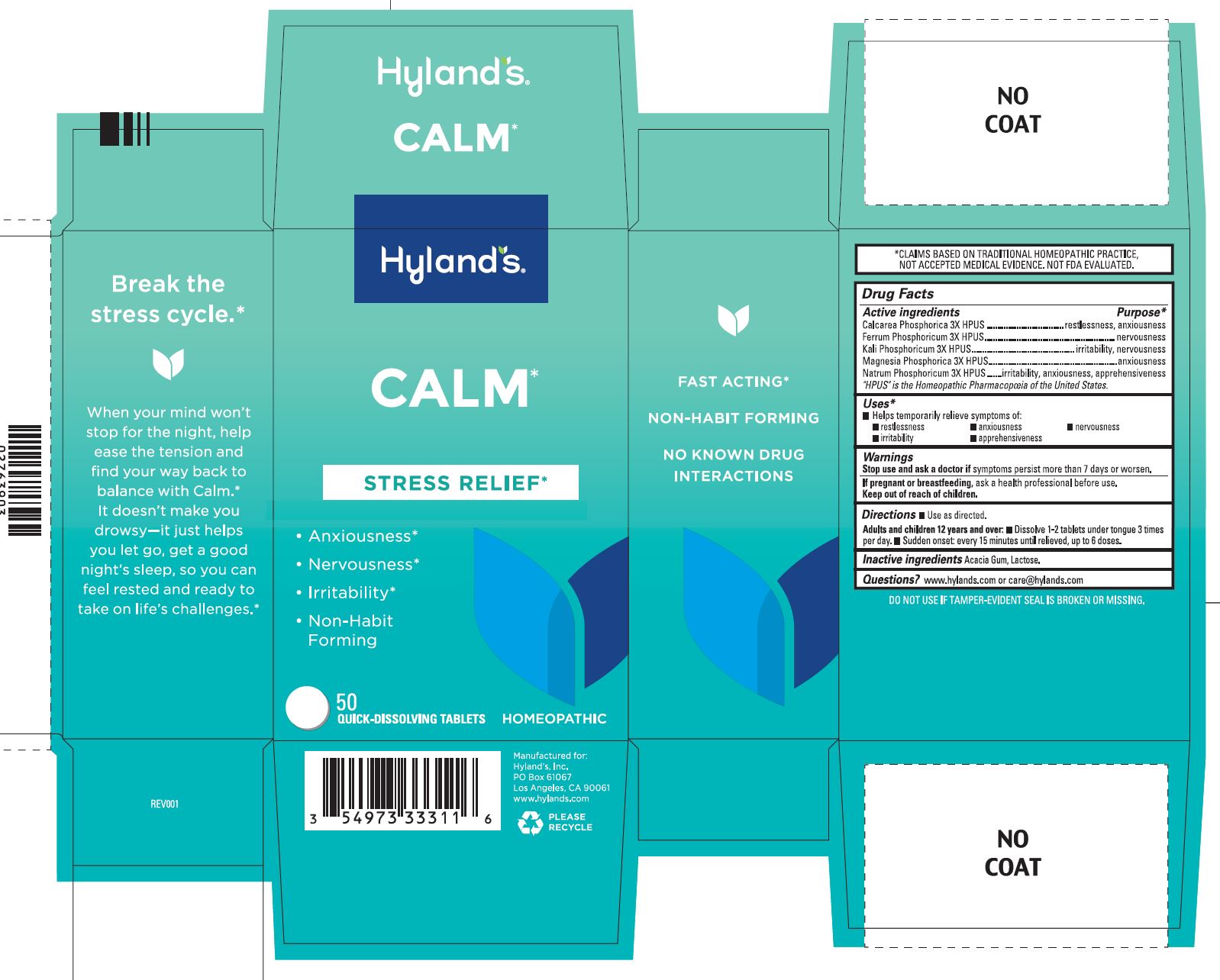 DRUG LABEL: Calm
NDC: 54973-3331 | Form: TABLET
Manufacturer: Hyland's Inc.
Category: homeopathic | Type: HUMAN OTC DRUG LABEL
Date: 20250319

ACTIVE INGREDIENTS: FERROSOFERRIC PHOSPHATE 3 [hp_X]/1 1; DIBASIC POTASSIUM PHOSPHATE 3 [hp_X]/1 1; MAGNESIUM PHOSPHATE, DIBASIC TRIHYDRATE 3 [hp_X]/1 1; SODIUM PHOSPHATE, DIBASIC, HEPTAHYDRATE 3 [hp_X]/1 1; TRIBASIC CALCIUM PHOSPHATE 3 [hp_X]/1 1
INACTIVE INGREDIENTS: ACACIA; LACTOSE MONOHYDRATE

Calm

PURPOSE

Natural relief of anxiousness, nervousness and irritability

Drug Facts

Active Ingredients | Purpose
Calcarea Phosphorica 3X HPUS | restlessness, anxiousness
Ferrum Phosphoricum 3X HPUS | nervousness
Kali Phosphoricum 3X HPUS | irritability, anxiousness, nervousness
Natrum Phosphoricum 3X HPUS | irritability, anxiousness and apprehensiveness
Magnesia Phosphorica 3X HPUS | anxiousness

Indications and Usage

■ Helps temporarily relieves symptoms of:
■ restlessness ■ anxiousness ■ nervousness
■ irritability ■ apprehensiveness

Warnings

Stop use and ask a doctor if

symptoms persist more than 7 days or worsen.

If pregnant or breastfeeding

ask a health professional before use.

Directions

■ Use as directed.

Adults and children 12 years and over: ■ Dissolve 1-2 tablets under tongue 3 times per day. ■ Sudden onset: every 15 minutes until relieved, up to 6 doses.

Inactive ingredients

Acacia Gum, Lactose.

Questions?

www.hylands.com or care@hylands.com

Indications and Usage (Uses)

■ Helps temporarily relieves symptoms of:

■ restlessness ■ anxiousness ■ nervousness

■ irritability  ■ apprehensiveness

Dosage and Administration (Directions)

Dissolve 1-2 tablets under tongue, up to 3 times per day.

Sudden onset: every 15 minutes until relieved, up to 6 doses.

Uses

■ Helps temporarily relieves symptoms of:

■ restlessness ■ anxiousness ■ nervousness

■ irritability ■ apprehensiveness

Principal Display Panel

Hyland's

NATURALS™

CALM

STRESS RELIEF*

- Anxiousness
- Nervousness
- Irritability
- Non-Habit

Forming

50

QUICK-DISSOLVING TABLETS